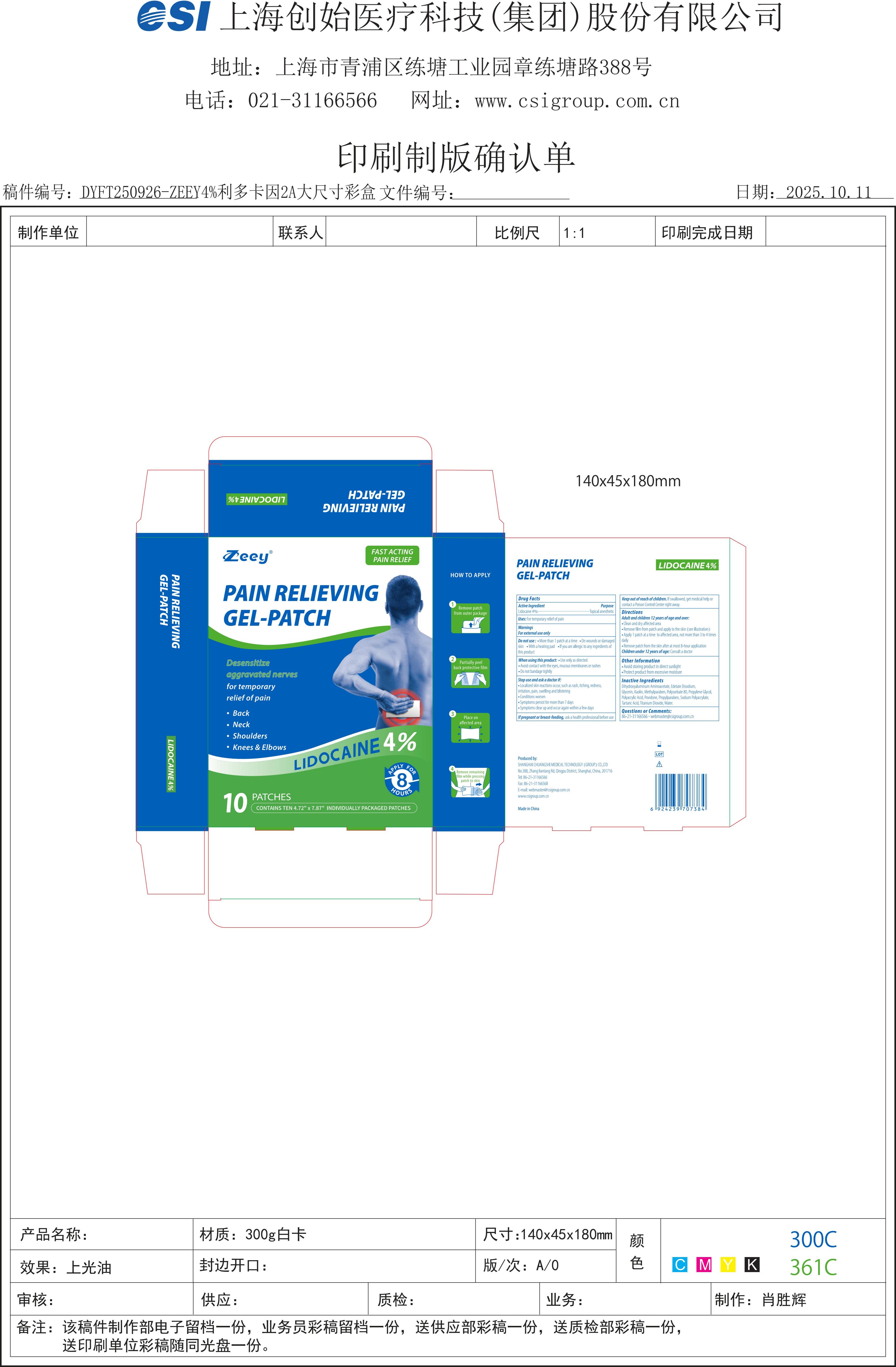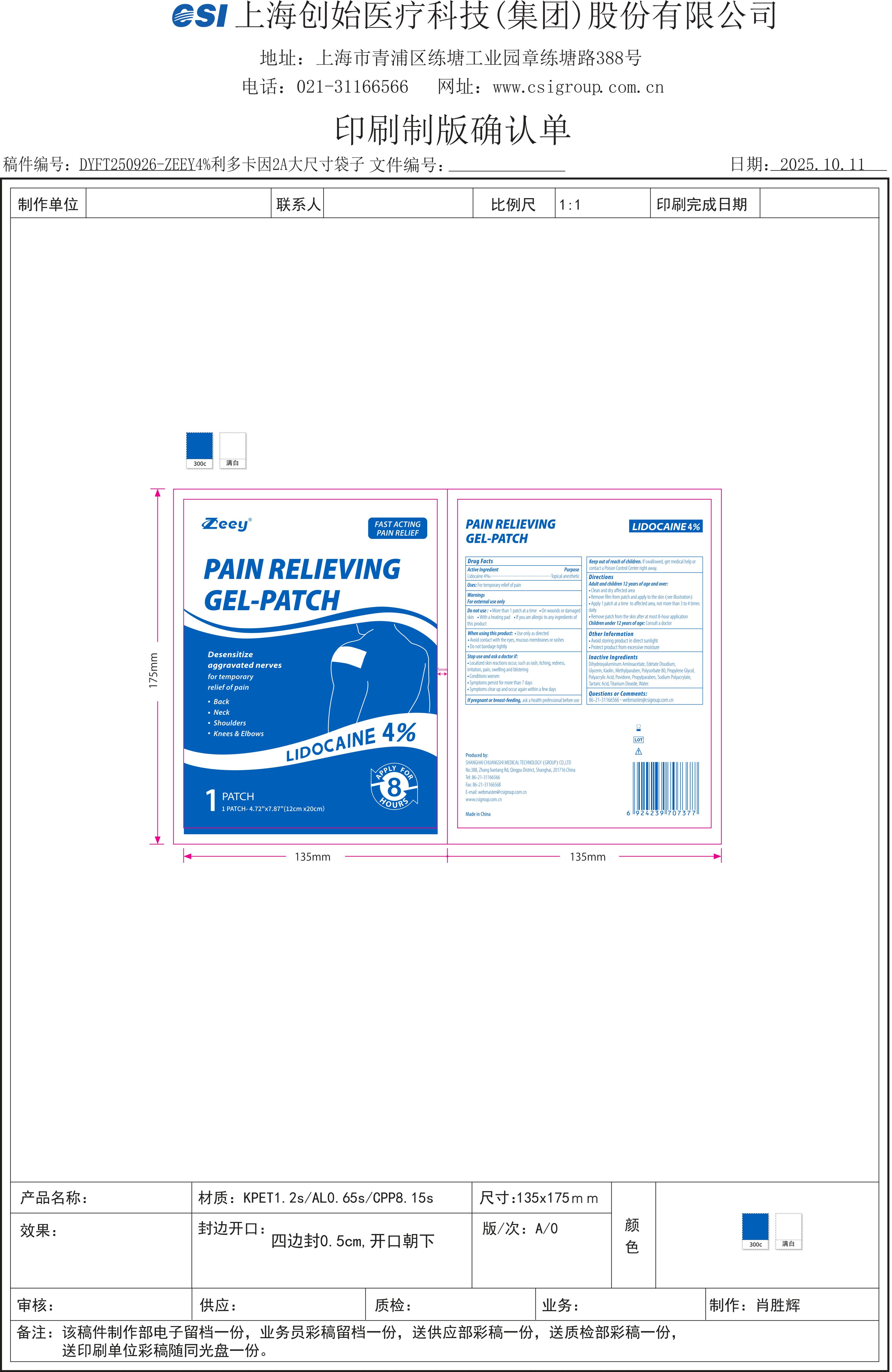 DRUG LABEL: Pain Relieving Gel-Patch
NDC: 73557-185 | Form: PATCH
Manufacturer: Shanghai Chuangshi Medical Technology (Group) Co., Ltd.
Category: otc | Type: HUMAN OTC DRUG LABEL
Date: 20251015

ACTIVE INGREDIENTS: LIDOCAINE 0.04 g/1 g
INACTIVE INGREDIENTS: POLYSORBATE 80; GLYCERIN; POVIDONE K90; METHYLPARABEN; PROPYLPARABEN; EDETATE DISODIUM; KAOLIN; TARTARIC ACID; WATER; PROPYLENE GLYCOL; POLYACRYLIC ACID (250000 MW); SODIUM POLYACRYLATE (2500000 MW); TITANIUM DIOXIDE; DIHYDROXYALUMINUM AMINOACETATE ANHYDROUS

73557-185

Active ingredient

Lidocaine 4% ...... Purpose: Topical Anesthetic

Purpose

Topical Anesthetic

Uses

For temporary relief of pain

Warnings

For external use only

Ask a doctor if:

- localized skin reactions occur, such as rash, itching, redness, irritation, pain, swelling and blistering
- Conditions worsen
- Symptoms persists for more than 7 days
- Symptoms clear up and occur again within a few days

When using this product

- Use only as directed
- Avoid contact with the eyes, mucous membranes or rashed
- Do not bandage tightly

Do not use

- More than 1 patch at a time
- On wounds or damaged skin
- With a heating pad
- If you are allergic to any ingredients of this product

Stop use if:

- localized skin reactions occur, such as rash, itching, redness, irritation, pain, swelling and blistering
- Conditions worsen
- Symptoms persists for more than 7 days
- Symptoms clear up and occur again within a few days

Pregnancy or breast feeding

If pregnant or breastfeeding, ask a health professional before use

Directions

Adult and Children 12 years of age and over:

- Clean and dry affected area
- Remove film from patch and apply to the skin (see illustration)
- Apply 1 patch at a time to affected area, not more than 3 to 4 times daily
- Remove patch from the skin after at most 8-hour application

Children under 12 years of age: Consult a doctor

Keep out of reach of children. If swallowed, get medical help or contact a Poison Control Center right away.

Inactive ingredients

Glycerin, Sodium Polyacrylate, Dihydroxyaluminum Aminoacetate, Disodium Ethylenediaminetetraacetic Acid, Kaolin, Titanium Dioxide, Polysorbate 80, Propylene Glycol, Tartaric Acid, Polyacrylic Acid, Povidone, Methylparaben, Propylparaben, Water

Questions or Comments?

86-21-31166566；webmaster@csigroup.com.cn

Other information

- Avoid storing product in direct sunlight
- Protect product from excessive moisture